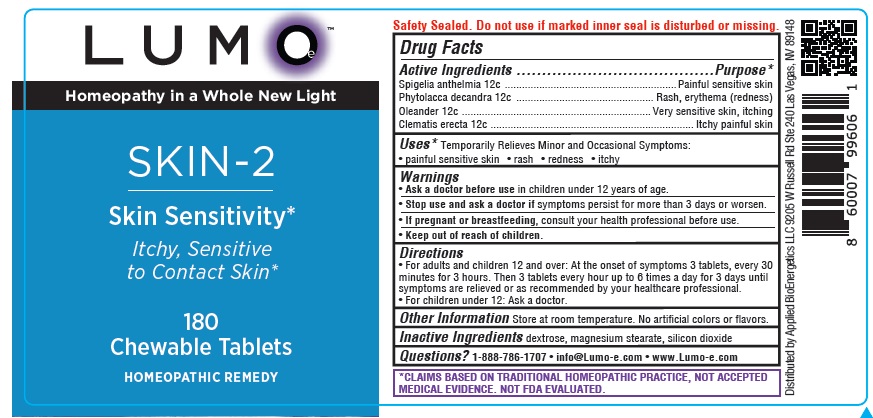 DRUG LABEL: LUMOe SKIN2 Skin Sensitivity
NDC: 81425-008 | Form: TABLET, CHEWABLE
Manufacturer: Applied Bioenergetics, LLC
Category: homeopathic | Type: HUMAN OTC DRUG LABEL
Date: 20251110

ACTIVE INGREDIENTS: SPIGELIA ANTHELMIA 12 [hp_C]/1 1; PHYTOLACCA AMERICANA ROOT 12 [hp_C]/1 1; NERIUM OLEANDER LEAF 12 [hp_C]/1 1; CLEMATIS RECTA FLOWERING TOP 12 [hp_C]/1 1
INACTIVE INGREDIENTS: DEXTROSE; MAGNESIUM STEARATE; SILICON DIOXIDE

LUMOe SKIN-2 Skin Sensitivity

Drug Facts

Active Ingredients
Spigelia anthelmia 12c
Phytolacca decandra 12c
Oleander 12c
Clematis erecta 12c

Purpose*
Spigelia anthelmia ............................................................ Painful sensitive skin
Phytolacca decandra ................................................ Rash, erythema (redness)
Oleander .................................................................. Very sensitive skin, itching
Clematis erecta ....................................................................... Itchy painful skin

INDICATIONS AND USAGE

Uses* Temporarily Relieves Minor and Occasional Symptoms:
• painful sensitive skin • rash • redness • itchy

Warnings
• Ask a doctor before use in children under 12 years of age.
• Stop use and ask a doctor if symptoms persist for more than 3 days or worsen.
• If pregnant or breastfeeding, consult your health professional before use.

• Keep out of reach of children.

Directions
• For adults and children 12 and over: At the onset of symptoms 3 tablets, every 30
minutes for 3 hours. Then 3 tablets every hour up to 6 times a day for 3 days until
symptoms are relieved or as recommended by your healthcare professional.
• For children under 12: Ask a doctor.

Other Information Store at room temperature. No artificial colors or flavors.

Inactive Ingredients dextrose, magnesium stearate, silicon dioxide

QUESTIONS

Questions? 1-888-786-1707 • info@Lumo-e.com • www.Lumo-e.com

*CLAIMS BASED ON TRADITIONAL HOMEOPATHIC PRACTICE, NOT ACCEPTED
MEDICAL EVIDENCE. NOT FDA EVALUATED.

LUMOe SKIN-2 Skin Sensitivity

LUMOe

Homeopathy in a Whole New Light

SKIN-2
Skin Sensitivity*

180
Chewable Tablets
HOMEOPATHIC REMEDY

Distributed by Applied BioEnergetics LLC 9205 W Russell Rd Ste 240 Las Vegas, NV 89148

res